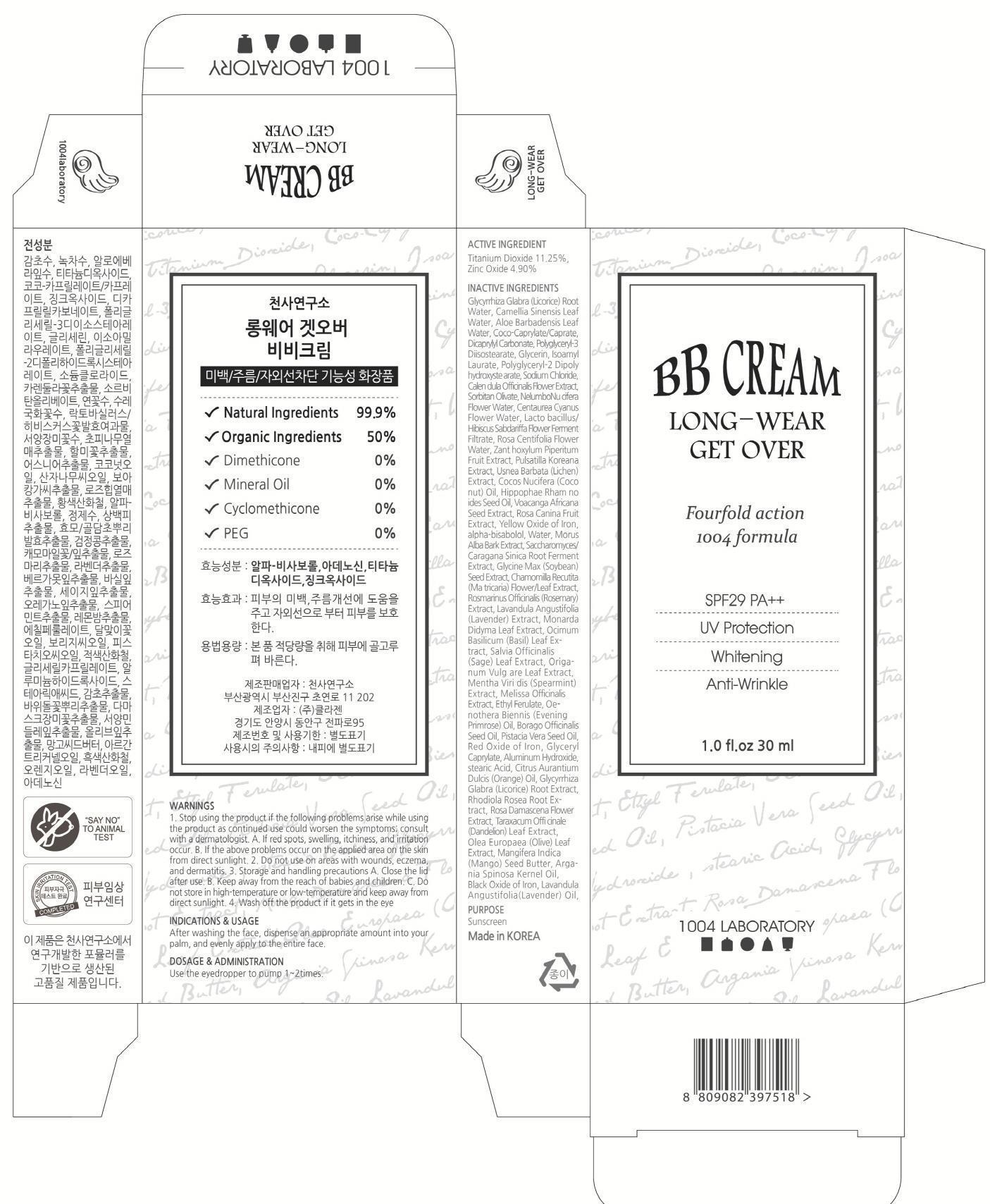 DRUG LABEL: LONG WEAR GET OVER BB
NDC: 69739-020 | Form: CREAM
Manufacturer: 1004LABORATORY
Category: otc | Type: HUMAN OTC DRUG LABEL
Date: 20150424

ACTIVE INGREDIENTS: Titanium Dioxide 3.37 mg/30 mL; Zinc Oxide 1.47 mg/30 mL
INACTIVE INGREDIENTS: Licorice

ACTIVE INGREDIENT

Active Ingredient: Titanium Dioxide 11.25%, Zinc Oxide 4.90%

INACTIVE INGREDIENT

Inactive Ingredients: Glycyrrhiza Glabra (Licorice) Root Water, Camellia Sinensis Leaf Water, Aloe Barbadensis Leaf Water, Coco-Caprylate/Caprate, Dicaprylyl Carbonate, Polyglyceryl-3 Diisostearate, Glycerin, Isoamyl Laurate, Polyglyceryl-2 Dipolyhydroxyste arate, Sodium Chloride, Calen dula Officinalis Flower Extract, Sorbitan Olivate, NelumboNu cifera Flower Water, Centaurea Cyanus Flower Water, Lacto bacillus/Hibiscus Sabdariffa Flower Ferment Filtrate, Rosa Centifolia Flower Water, Zant hoxylum Piperitum Fruit Ext ract, Pulsatilla Koreana Extract, Usnea Barbata (Lichen) Extract, Cocos Nucifera (Coco nut) Oil, Hippophae Rham no ides Seed Oil, Voacanga Afri cana Seed Extract, Rosa Cani na Fruit Extract, Yellow Oxide of Iron, alpha-bisabolol, Water, Morus Alba Bark Extract, Saccharomyces/Caragana Sinica Root Ferment Extract, Glycine Max (Soybean) Seed Extract, Chamomilla Recutita (Ma tricaria) Flower/Leaf Extract, Rosmarinus Officinalis (Rosemary) Extract, Lavandula Angustifolia (Lavender) Extract, Monarda Didyma Leaf Extract, Ocimum Basilicum (Basil) Leaf Extract, Salvia Officinalis (Sage) Leaf Extract, Origanum Vulg are Leaf Extract, Mentha Viri dis (Spearmint) Extract, Melissa Officinalis Extract, Ethyl Ferulate, Oenothera Biennis (Evening Primrose) Oil, Borago Officinalis Seed Oil, Pistacia Vera Seed Oil, Red Oxide of Iron, Glyceryl Caprylate, Aluminum Hydroxide, stearic Acid, Citrus Aurantium Dulcis (Orange) Oil, Glycyrrhiza Glabra (Licorice) Root Extract, Rhodiola Rosea Root Extract, Rosa Damascena Flower Extract, Taraxacum Offi cinale (Dandelion) Leaf Extract, Olea Europaea (Olive) Leaf Extract, Mangifera Indica (Mango) Seed Butter, Argania Spinosa Kernel Oil, Black Oxide of Iron, Lavandula Angustifolia(Lavender) Oil, Adenosine

PURPOSE

Purpose: Sunscreen

WARNINGS

Warnings: 1. Stop using the product if the following problems arise while using the product as continued use could worsen the symptoms; consult with a dermatologist. A. If red spots, swelling, itchiness, and irritation occur. B. If the above problems occur on the applied area on the skin from direct sunlight 2. Do not use on areas with wounds, eczema, and dermatitis. 3. Storage and handling precautions A. Close the lid after use. B. Keep away from the reach of babies and children. C. Do not store in high-temperature or low-temperature and keep away from direct sunlight 4. Wash off the product if it gets in the eye

DESCRIPTION

Indications & Usage: After washing the face, dispense an appropriate amount into your palm, and evenly apply to the entire face.

Dosage & Administration: Use the eyedropper to pump 1~2times.